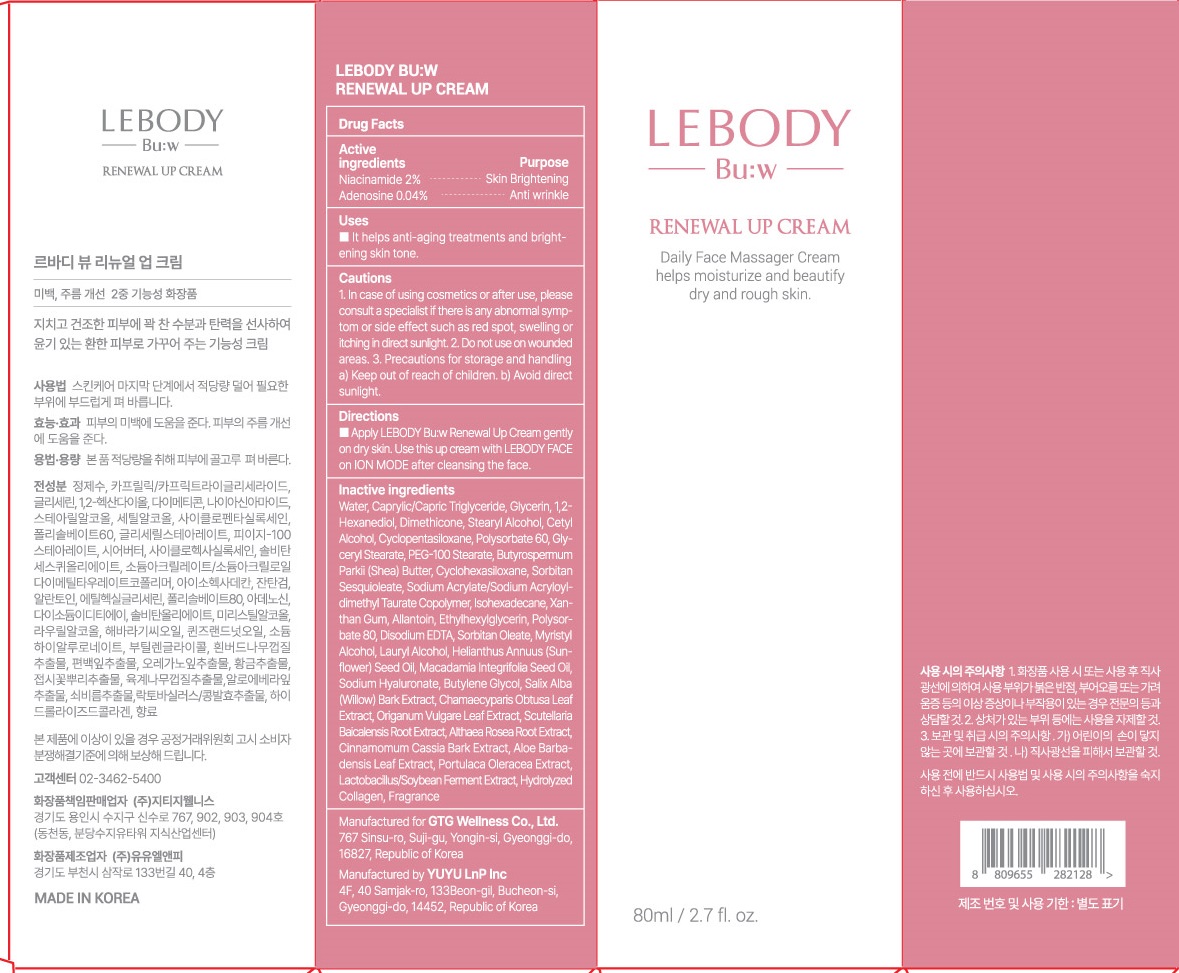 DRUG LABEL: LEBODY BU W RENEWAL UP
NDC: 71080-0003 | Form: CREAM
Manufacturer: GTG Wellness Co., Ltd.
Category: otc | Type: HUMAN OTC DRUG LABEL
Date: 20230224

ACTIVE INGREDIENTS: Niacinamide 1.6 g/80 mL; Adenosine 0.03 g/80 mL
INACTIVE INGREDIENTS: Water; Propylene Glycol

ACTIVE INGREDIENTS

Niacinamide 2%

Adenosine 0.04%

INACTIVE INGREDIENTS

Water, Caprylic/Capric Triglyceride, Glycerin, 1,2-Hexanediol, Dimethicone, Stearyl Alcohol, Cetyl Alcohol, Cyclopentasiloxane, Polysorbate 60, Glyceryl Stearate, PEG-100 Stearate, Butyrospermum Parkii (Shea) Butter, Cyclohexasiloxane, Sorbitan Sesquioleate, Sodium Acrylate/Sodium Acryloyldimethyl Taurate Copolymer, Isohexadecane, Xanthan Gum, Allantoin, Ethylhexylglycerin, Polysorbate 80, Disodium EDTA, Sorbitan Oleate, Myristyl Alcohol, Lauryl Alcohol, Helianthus Annuus (Sunflower) Seed Oil, Macadamia Integrifolia Seed Oil, Sodium Hyaluronate, Butylene Glycol, Salix Alba (Willow) Bark Extract, Chamaecyparis Obtusa Leaf Extract, Origanum Vulgare Leaf Extract, Scutellaria Baicalensis Root Extract, Althaea Rosea Root Extract, Cinnamomum Cassia Bark Extract, Aloe Barbadensis Leaf Extract, Portulaca Oleracea Extract, Lactobacillus/Soybean Ferment Extract, Hydrolyzed Collagen, Fragrance

PURPOSE

Skin Brightening

Anti wrinkle

Cautions

1. In case of using cosmetics or after use, please consult a specialist if there is any abnormal symptom or side effect such as red spot, swelling or itching in direct sunlight.
2. Do not use on wounded areas.
3. Precautions for storage and handling
a) Keep out of reach of children.
b) Avoid direct sunlight.

KEEP OUT OF REACH OF CHILDREN

Keep out of reach for children.

Uses

It helps anti-aging treatments and brightening skin tone.

Directions

■ Apply LEBODY Bu:w Renewal Up Cream gently on dry skin. Use this up cream with LEBODY FACE on ION MODE after cleansing the face.